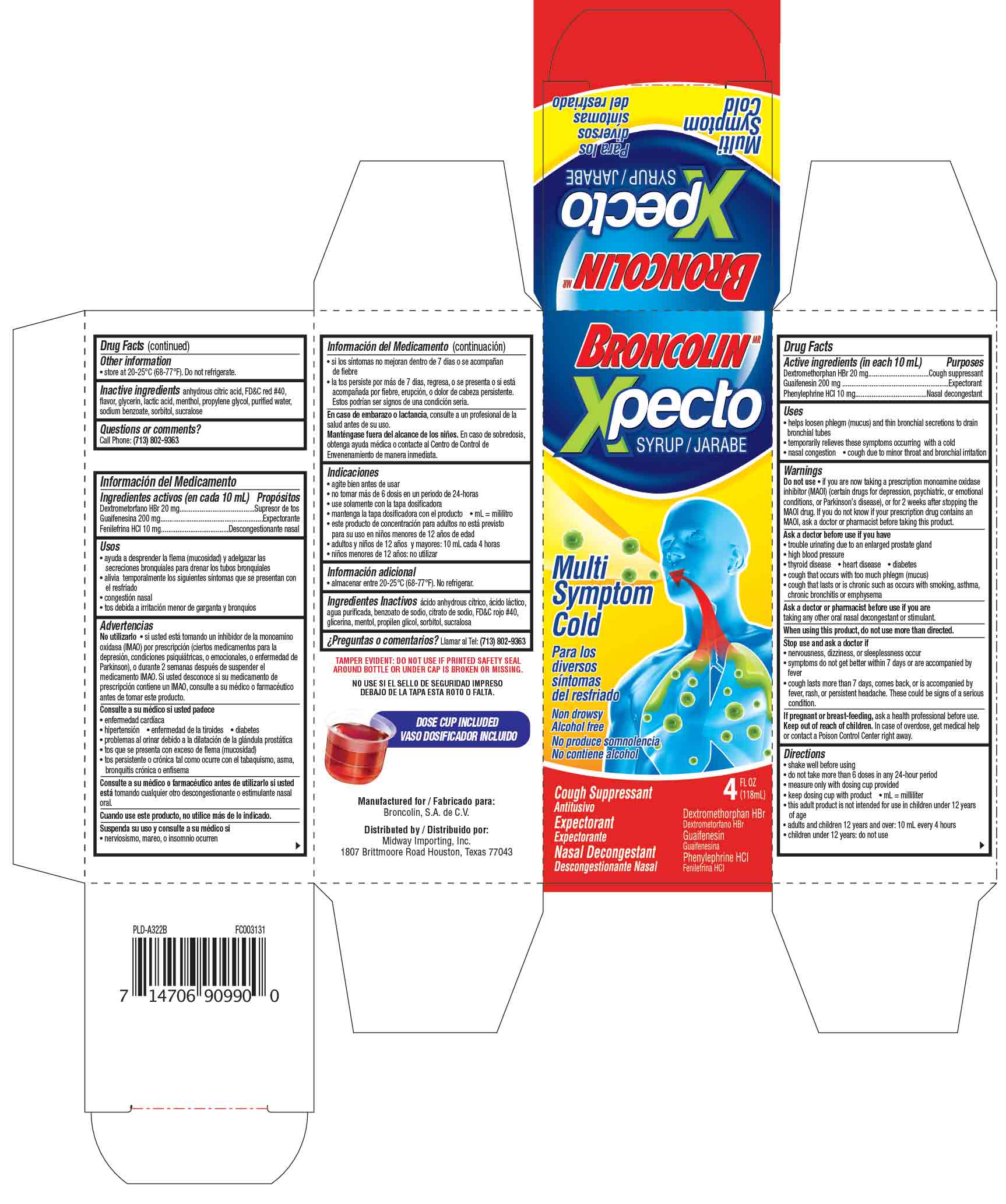 DRUG LABEL: Xpecto
NDC: 76095-005 | Form: SYRUP
Manufacturer: MIDWAY IMPORTING INC
Category: otc | Type: HUMAN OTC DRUG LABEL
Date: 20170817

ACTIVE INGREDIENTS: GUAIFENESIN 200 mg/10 mL; PHENYLEPHRINE HYDROCHLORIDE 10 mg/10 mL; DEXTROMETHORPHAN HYDROBROMIDE 20 mg/10 mL
INACTIVE INGREDIENTS: ANHYDROUS CITRIC ACID; FD&C RED NO. 40; SORBITOL; GLYCERIN; LACTIC ACID; MENTHOL; PROPANEDIOL; WATER; SODIUM BENZOATE; SUCRALOSE

Drug Facts

Active ingredient (in each 10 mL)

Dextromethorphan HBr 20 mg

Guaifenesin 200 mg

Phenylephrine HCl 10 mg

Purposes

Cough suppressant

Expectorant

Nasal Decongestant

Uses

- helps loosen phlegm (mucus) and thin bronchial secretions to drain bronchial tubes
- temporarily relieves these symptoms occurring with a cold
- nasal congestion
- cough due to minor throat and bronchial irritation

Warnings

Do not use • if you are now taking a prescription monoamine oxidase inhibitor (MAOI) (certain drugs for depression, psychiatric, or emotional conditions, or Parkinson's disease), or for 2 weeks after stopping the MAOI drug. If you do not know if your prescription drug contains an MAOI, ask a doctor or pharmacist before taking this product.

Ask a doctor before use if you have

- trouble urinating due to enlarged prostate gland
- high blood pressure
- thyroid disease • heart disease • diabetes
- cough that occurs with too much phlegm (mucus)
- cough that lasts or is chronic such as occurs with smoking, asthma, chronic bronchitis or emphysema

Ask a doctor or pharmacist before use if you are

taking any other oral nasal decongestant or stimulant

When using this product

do not use more than directed

Stop use and ask a doctor if

- nervousness, dizziness, or sleeplessness occur
- symptoms do not get better within 7 days or are accompanied by fever
- cough lasts more than 7 days, comes back, or is accompanied by fever, rash, or persistent headache. These could be signs of a serious condition

If pregnant or breast-feeding

ask a health professional before

Keep out of reach of children

In case of overdose, get medical help or contact a Poison Control Center right away.

Directions

- shake well before using
- do not take more than 4 doses in any 24-hour period
- measure only with dosing cup provided
- keep dosing cup with product mL=milliliter
- this adult product is not intended for use in children under 12 years of age
- adults and children 12 years and over: 10mL every 4 hours
- children under 12 years: do not use

Other information

- store at 20C-25C (68F-77F). Do not refrigerate

Inactive ingredients

anhydrous citric acid,FD&C Red #40, flavor, glycerin, lactic acid, menthol, propylene glycol, purified water, sodium benzoate, sorbitol, sucralose

Questions or comments?

Call 703-802-9363